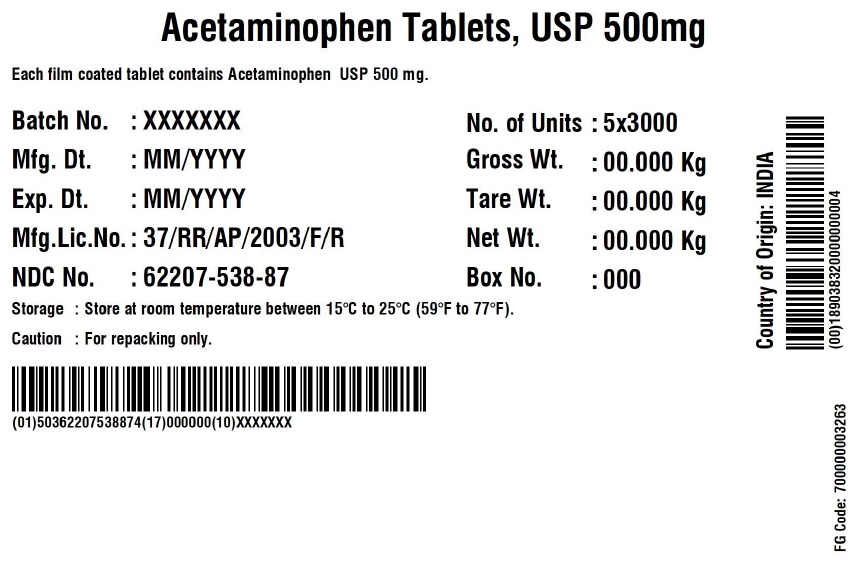 DRUG LABEL: Acetaminophen 500 mg
NDC: 62207-538 | Form: TABLET
Manufacturer: Granules India Limited
Category: otc | Type: HUMAN OTC DRUG LABEL
Date: 20230127

ACTIVE INGREDIENTS: ACETAMINOPHEN 500 mg/1 1
INACTIVE INGREDIENTS: POLYETHYLENE GLYCOL, UNSPECIFIED; STEARIC ACID; LECITHIN, SOYBEAN; FD&C RED NO. 40; POVIDONE K30; FD&C YELLOW NO. 6; STARCH, CORN; SUCRALOSE; TALC; TITANIUM DIOXIDE

Acetaminophen tablets USP 500 mg (Round)